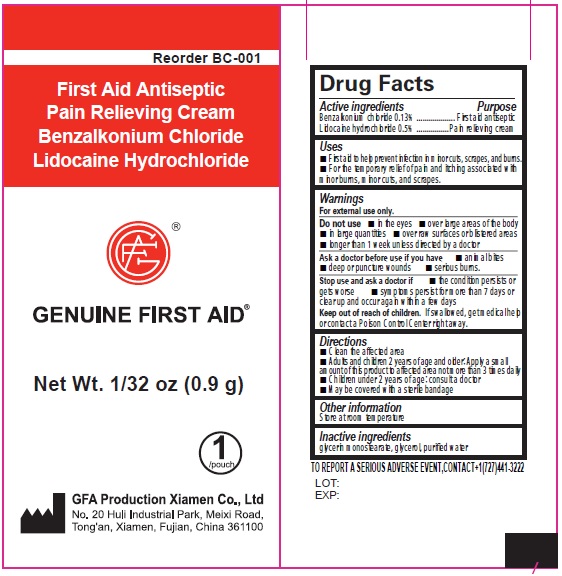 DRUG LABEL: Genuine First Aid First Aid Antiseptic Pain Relieving Cream
NDC: 50814-059 | Form: CREAM
Manufacturer: GFA Production (Xiamen) Co., Ltd.
Category: otc | Type: HUMAN OTC DRUG LABEL
Date: 20241015

ACTIVE INGREDIENTS: BENZALKONIUM CHLORIDE 1.3 mg/1 g; LIDOCAINE HYDROCHLORIDE 5 mg/1 g
INACTIVE INGREDIENTS: GLYCERIN; WATER

Genuine First Aid First Aid Antiseptic Pain Relieving Cream

Active ingredients

Benzalkonium chloride 0.13%

Lidocaine hydrochloride 0.5%

Purpose

First aid antiseptic

Pain relieving cream

Uses

- First aid to help prevent infection in minor cuts, scrapes, and burns.
- For the temporary relief of pain and itching associated with minorburns, minorcuts, and scrapes.

Warnings

For external use only.

Do not use

- in the eyes.
- over large areas of the body
- in large quantities
- over raw surfaces or listed areas
- longer than 1 week unless directed by a doctor

Ask a doctor before use if you have

- animals bites
- deep or puncture wounds
- serious burns.

Stop use and ask a doctor if

- the condition persists or gets worse
- symptoms persists for more than 7 days or clearup and occurs again with in a few days

Keep out of reach of children.

If swallowed, get medical help or contact a Poison Control Center right away.

Directions

- Clean the affected area.
- Adults and children 2 years of age and older. Apply a small amount of this product to affected area not more than 3 times daily
- Children under 2 years of age:consult a doctor
- May be covered with a sterile bandage.

Other information

Store at room temperature

Inactive ingredients

glycerin monostearate, glycerol, purified water